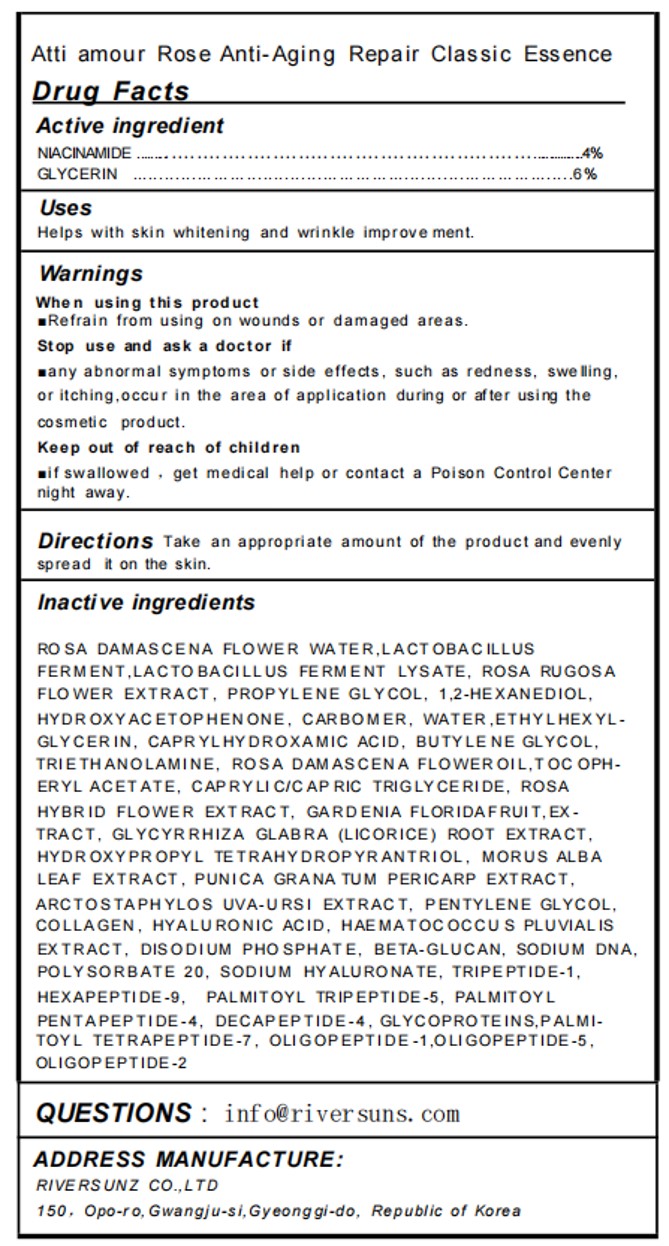 DRUG LABEL: Atti amour Rose Anti-Aging Repair Classic Essence
NDC: 84601-001 | Form: LIQUID
Manufacturer: RIVER SUNZ co.,Ltd
Category: otc | Type: HUMAN OTC DRUG LABEL
Date: 20251106

ACTIVE INGREDIENTS: GLYCERIN 6 g/100 mL; NIACINAMIDE 4 g/100 mL
INACTIVE INGREDIENTS: ROSA DAMASCENA FLOWER OIL; MORUS ALBA LEAF; TROLAMINE; DIMETHICONE/VINYL DIMETHICONE CROSSPOLYMER (HARD PARTICLE); HAEMATOCOCCUS PLUVIALIS; SODIUM PYRROLIDONE CARBOXYLATE; ETHYLHEXYLGLYCERIN; CARBOXYPOLYMETHYLENE; POLYSORBATE 20; PENTYLENE GLYCOL; BUTYLENE GLYCOL; PALMITOYL TETRAPEPTIDE-7; HYDROXYPROPYL TETRAHYDROPYRANTRIOL; WATER; CAPRYLHYDROXAMIC ACID; ROSA RUGOSA FLOWER; 1,2-HEXANEDIOL; HEXAPEPTIDE-9; PALMITOYL TRIPEPTIDE-5; LACTOBACILLUS REUTERI F275 STRAIN; PALMITOYL PENTAPEPTIDE-4; ALPHA-TOCOPHEROL ACETATE; ARCTOSTAPHYLOS UVA-URSI WHOLE; ALLANTOIN; GLYCOPROTEIN IIB/IIIA; PROPYLENE GLYCOL; MEDIUM-CHAIN TRIGLYCERIDES; SODIUM PHOSPHATE, DIBASIC, ANHYDROUS; HYALURONIC ACID; PREZATIDE; POMEGRANATE FRUIT RIND; HYALURONATE SODIUM; SODIUM CARBOXYMETHYL .BETA.-GLUCAN (DS 0.65-0.85); HYDROXYACETOPHENONE; GLYCYRRHIZA GLABRA; GARDENIA JASMINOIDES FRUIT; HYDROLYZED WHEAT PROTEIN (ENZYMATIC, 3000 MW); MARINE COLLAGEN, SOLUBLE

84601-001 Atti amour Rose Anti-Aging Repair Classic Essence

ACTIVE INGREDIENT

NIACINAMIDE 4%
GLYCERIN 6%

PURPOSE

Heips with skin whitening and wrinkle improve ment.

KEEP OUT OF REACH OF CHILDREN

if swallowed , get medical help or contact a Poison Control Center night away.

INDICATIONS AND USAGE

Heips with skin whitening and wrinkle improve ment.

WARNINGS

For external use only
When using this product
Refrain from using on wounds or damaged areas.
Stop use and ask a doctor if
any abnormal symptoms or side effects, such as redness, swe llingor itching,occur in the area of application during or after using the cosmetic product.
Keep out of reach of children
ifswallowed , get medical help or contact a Poison Control Centernight away.

DOSAGE AND ADMINISTRATION

Directions Take an appropriate amount of the product and evenlyspread it on the skin.

STORAGE AND HANDLING

Store in a cool and dark place away from light

INACTIVE INGREDIENT

ROSA DAMASCENA FLOWER WATER
LACTOBACILLUS FERMENT
LACTOBACILLUS FERMENT LYSATE
ROSA RUGOSA FLOWER EXTRACT
HYDROXYACETOPHENONE
1,2-HEXANEDIOL
TRIPEPTIDE-1
HEXAPEPTIDE-9
PALMITOYL TRIPEPTIDE-5
PALMITOYL PENTAPEPTIDE-4
PALMITOYL TETRAPEPTIDE-7
GLYCYRRHIZA GLABRA (LICORICE) ROOT EXTRACT
MORUS ALBA LEAF EXTRACT
PUNICA GRANATUM PERICARP EXTRACT
ARCTOSTAPHYLOS UVA-URSI EXTRACT
SODIUM HYALURONATE
HYDROXYPROPYL TETRAHYDROPYRANTRIOL
DECAPEPTIDE-4
GLYCOPROTEINS
PROPYLENE GLYCOL
BETA-GLUCAN
ROSA HYBRID FLOWER EXTRACT
GARDENIA FLORIDA FRUIT EXTRACT
TRIETHANOLAMINE
ROSA DAMASCENA FLOWER OIL
OLIGOPEPTIDE-1
OLIGOPEPTIDE-5
OLIGOPEPTIDE-2
COLLAGEN
HYALURONIC ACID
HAEMATOCOCCUS PLUVIALIS EXTRACT
CAPRYLIC/CAPRIC TRIGLYCERIDE
PENTYLENE GLYCOL
SODIUM DNA
CAPRYLHYDROXAMIC ACID
ETHYLHEXYLGLYCERIN
WATER
CARBOMER
BUTYLENE GLYCOL
POLYSORBATE 20
DISODIUM PHOSPHATE
TOCOPHERYL ACETATE